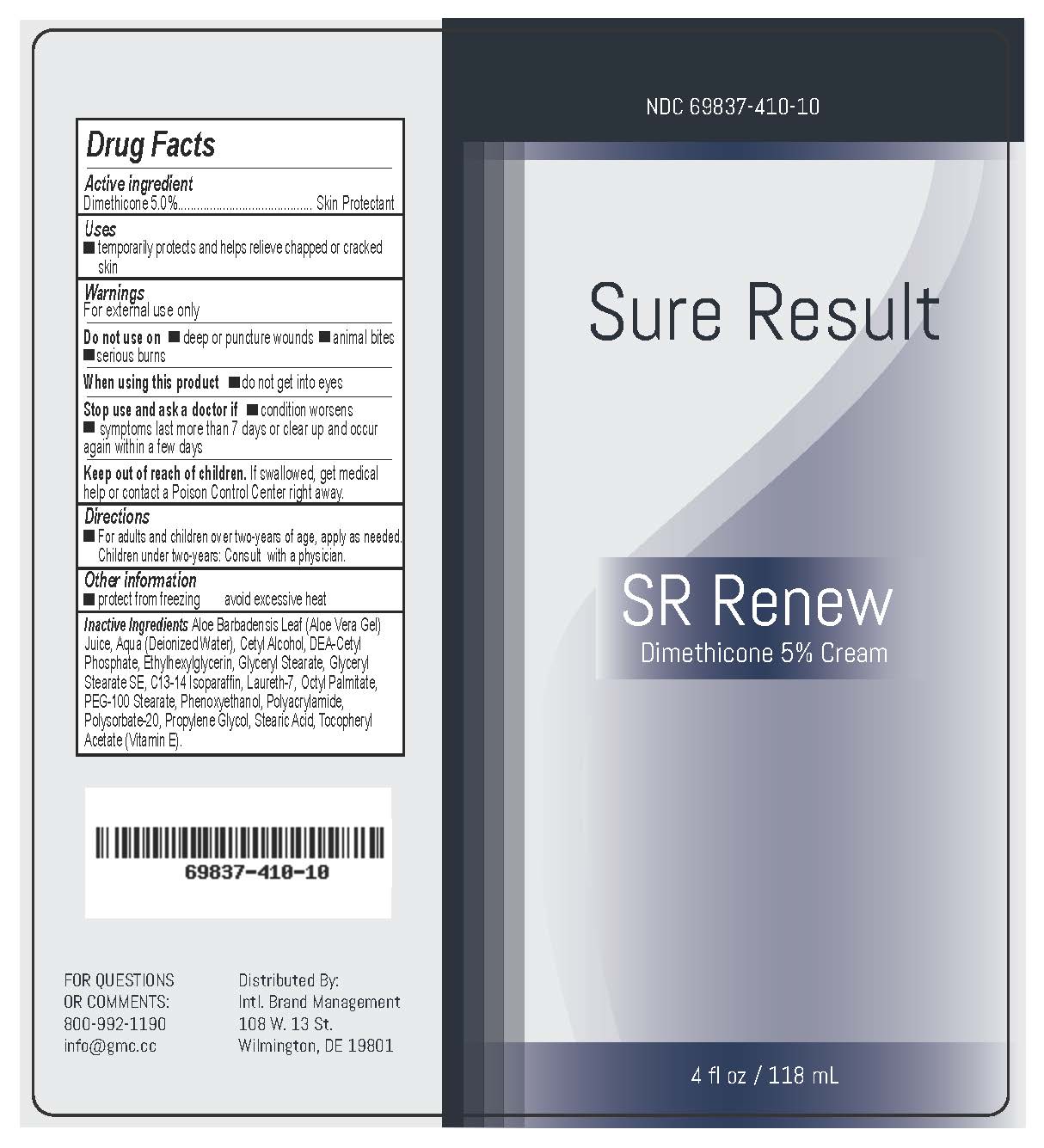 DRUG LABEL: Sure Result SR Renew
NDC: 69837-410 | Form: CREAM
Manufacturer: International Brand Management, LLC
Category: otc | Type: HUMAN OTC DRUG LABEL
Date: 20170623

ACTIVE INGREDIENTS: DIMETHICONE 50 mg/1 mL
INACTIVE INGREDIENTS: ALOE VERA LEAF; WATER; CETYL ALCOHOL; DIETHANOLAMINE CETYL PHOSPHATE; ETHYLHEXYLGLYCERIN; GLYCERYL MONOSTEARATE; C13-14 ISOPARAFFIN; LAURETH-7; ETHYLHEXYL PALMITATE; PEG-100 STEARATE; PHENOXYETHANOL; POLYACRYLAMIDE (10000 MW); POLYSORBATE 20; PROPYLENE GLYCOL; STEARIC ACID; .ALPHA.-TOCOPHEROL ACETATE, DL- 

Drug Facts

Active ingredient

Dimethicone 5.0%

PURPOSE

Skin Protectant

Uses

-temporarily protects and help relieve chapped or cracked skin

Warnings

For external use only

Do not use on -deep or puncture wounds -animal bites

-serious burns

When using this product -do not get into eyes

Stop use and ask a doctor if -condition worsens

-symptoms last more than 7 days or clear up and occur

again within a few days

Keep out of reach of children. If swallowed, get medical

help or contact a Poison Control Center right away.

Directions

-apply cream liberally as needed.

Other information

-protect from freezing avoid excessive heat

Inactive Ingredients Aloe Barbadensis Leaf (Aloe Vera Gel)

Juice, Aqua (Deionized Water), Cetyl Alcohol, DEA-Cetyl

Phosphate, Ethylhexylglycerin, Glyceryl Stearate, Glyceryl

Stearate SE, C13-14 Isoparaffin, Laureth-7, Octyl Palmitate,

PEG-100 Stearate, Phenoxyethanol, Polyacrylamide,

Polysorbate-20, Propylene Glycol, Stearic Acid, Tocopheryl

Acetate (Vitamin E).